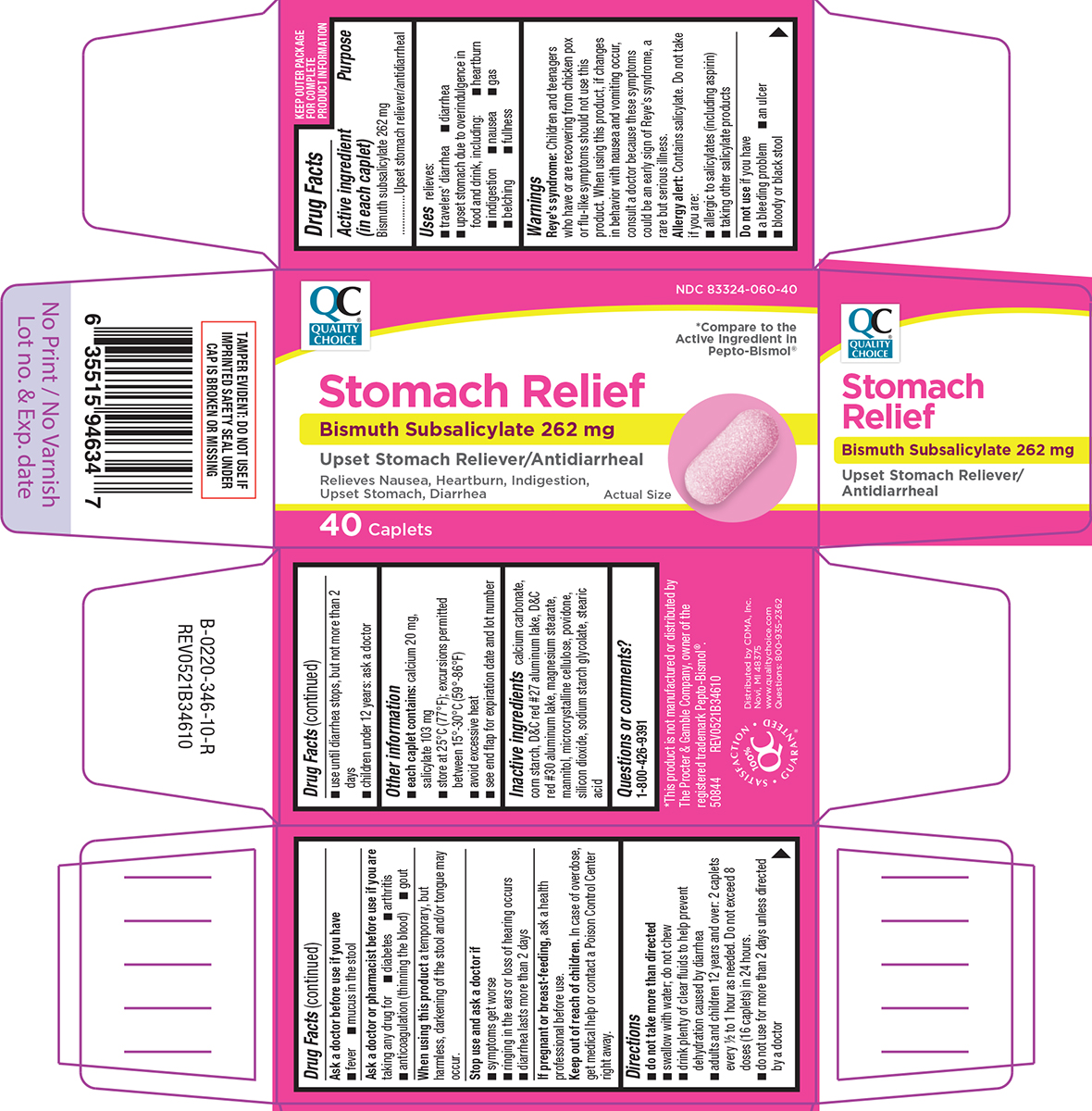 DRUG LABEL: Stomach Relief
NDC: 83324-060 | Form: TABLET
Manufacturer: Chain Drug Marketing Association, Inc.
Category: otc | Type: HUMAN OTC DRUG LABEL
Date: 20260226

ACTIVE INGREDIENTS: BISMUTH SUBSALICYLATE 262 mg/1 1
INACTIVE INGREDIENTS: CALCIUM CARBONATE; STARCH, CORN; D&C RED NO. 27 ALUMINUM LAKE; D&C RED NO. 30 ALUMINUM LAKE; MAGNESIUM STEARATE; MANNITOL; MICROCRYSTALLINE CELLULOSE; POVIDONE, UNSPECIFIED; SILICON DIOXIDE; SODIUM STARCH GLYCOLATE TYPE A POTATO; STEARIC ACID

Quality Choice 44-346

Active ingredient (in each caplet)

Bismuth subsalicylate 262 mg

Purpose

Upset stomach reliever/antidiarrheal

Uses

relieves:

- travelers' diarrhea
- diarrhea
- upset stomach due to overindulgence in food and drink, including:
  - belching
  - indigestion
  - gas
  - fullness
  - heartburn
  - nausea

Warnings

Reye's syndrome: Children and teenagers who have or are recovering from chicken pox or flu-like symptoms should not use this product. When using this product, if changes in behavior with nausea and vomiting occur, consult a doctor because these symptoms could be an early sign of Reye's syndrome, a rare but serious illness.

Allergy alert: Contains salicylate. Do not take if you are:

- allergic to salicylates (including aspirin)
- taking other salicylate products

Do not use

if you have

- an ulcer
- a bleeding problem
- bloody or black stool

Ask a doctor before use if you have

- fever
- mucus in the stool

Ask a doctor or pharmacist before use if you are

taking any drug for

- diabetes
- arthritis
- anticoagulation (thinning the blood)
- gout

When using this product

a temporary, but harmless, darkening of the stool and/or tongue may occur.

Stop use and ask a doctor if

- symptoms get worse
- ringing in the ears or loss of hearing occurs
- diarrhea lasts more than 2 days

If pregnant or breast-feeding,

ask a health professional before use.

Keep out of reach of children.

In case of overdose, get medical help or contact a Poison Control Center right away.

Directions

- do not take more than directed
- swallow with water; do not chew
- drink plenty of clear fluids to help prevent dehydration caused by diarrhea
- adults and children 12 years and over: 2 caplets every 1/2 to 1 hour as needed. Do not exceed 8 doses (16 caplets) in 24 hours.
- do not use for more than 2 days unless directed by a doctor
- use until diarrhea stops, but not more than 2 days
- children under 12 years: ask a doctor

Other information

- each caplet contains: calcium 20 mg, salicylate 103 mg
- store at 25ºC (77ºF); excursions permitted between 15º-30ºC (59º-86ºF)
- avoid excessive heat
- see end flap for expiration date and lot number

Inactive ingredients

calcium carbonate, corn starch, D&C red #27 aluminum lake, D&C red #30 aluminum lake, magnesium stearate, mannitol, microcrystalline cellulose, povidone, silicon dioxide, sodium starch glycolate, stearic acid

Questions or comments?

1-800-426-9391

Principal display panel

QC®
QUALITY
CHOICE

NDC 83324-060-40

*Compare to the
Active Ingredient in
Pepto-Bismol®

Stomach Relief
Bismuth Subsalicylate 262 mg
Upset Stomach Reliever/Antidiarrheal

Relieves Nausea, Heartburn, Indigestion,
Upset Stomach, Diarrhea

40 Caplets

Actual Size

TAMPER EVIDENT: DO NOT USE IF
IMPRINTED SAFETY SEAL UNDER
CAP IS BROKEN OR MISSING

*This product is not manufactured or distributed by
The Procter & Gamble Company, owner of the
registered trademark Pepto-Bismol®.
50844 REV0521B34610

Distributed by CDMA, Inc.
Novi, MI 48375
www.qualitychoice.com
Questions: 800-935-2362

SATISFACTION
100%
GUARANTEED®

Quality Choice 44-346